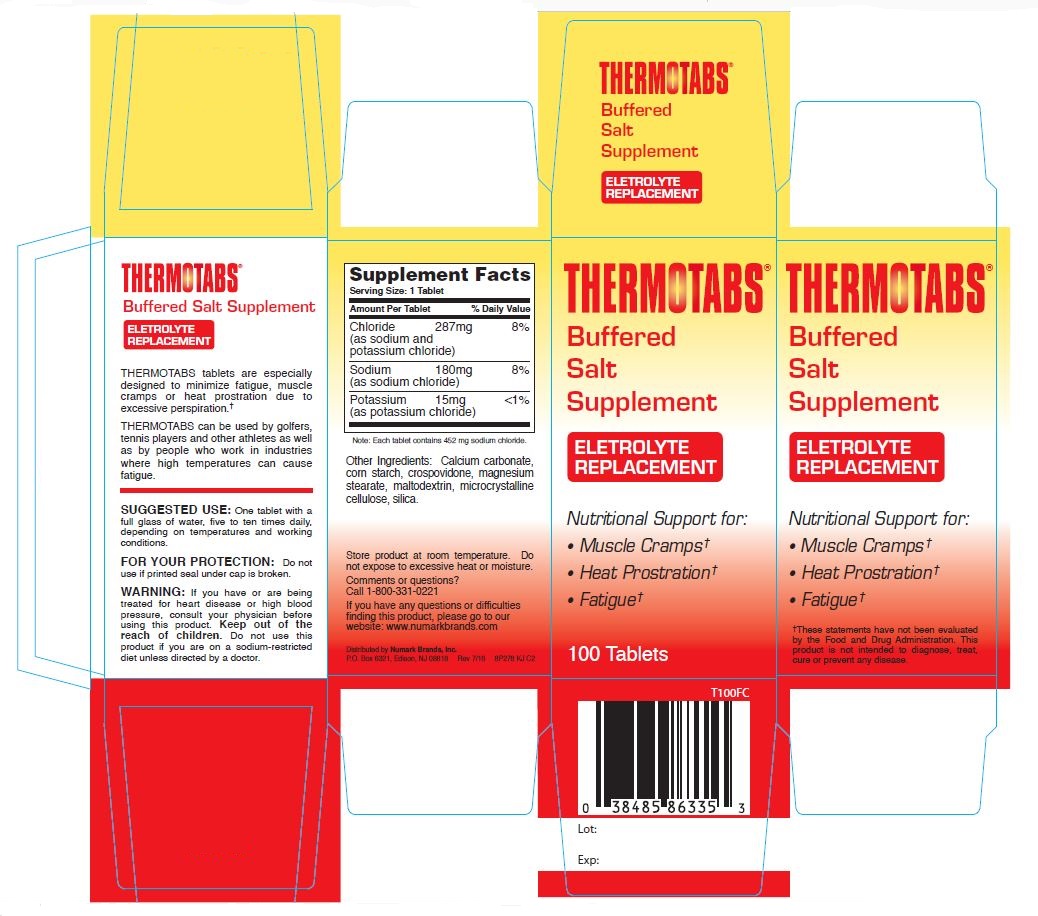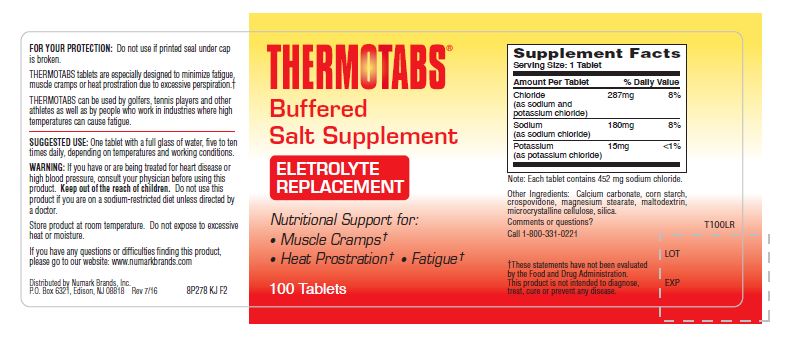 DRUG LABEL: Thermotabs Buffered Salt Supplement 
NDC: 69846-863 | Form: TABLET
Manufacturer: NUMARK BRANDS, INC
Category: other | Type: DIETARY SUPPLEMENT
Date: 20160802

ACTIVE INGREDIENTS: Sodium Chloride 454 mg/1 1; Potassium Chloride 30 mg/1 1
INACTIVE INGREDIENTS: Calcium Carbonate; Starch, Corn; Crospovidone; Magnesium Stearate; Maltodextrin; Cellulose, Microcrystalline; Silicon Dioxide

Thermotabs Buffered Salt Supplement

Supplement Facts

Serving Size: 1 Tablet

Amount Per Tablet |  | % Daily Value
Chloride (as sodium and potassium chloride) | 287mg | 8%
Sodium (as sodium chloride) | 180mg | 8%
Potassium (as potassium chloride) | 15mg | <1%
Note: Each tablet contains 452 mg sodium chloride.

Other Ingredients: Calcium carbonate, corn starch, crospovidone, magnesium stearate, maltodextrin, microcrystalline cellulose, silica.

HEALTH CLAIM

ELETROLYTE REPLACEMENT

Nutritional Support for:

- Muscle Cramps†
- Heat Prostration†
- Fatigue†

THERMOTABS tablets are especially designed to minimize fatigue, muscle cramps or heat prostration due to excessive perspiration.†

THERMOTABS can be used by golfers, tennis players and other athletes as well as by people who work in industries where high temperatures can cause fatigue.

†These statements have not been evaluated by the Food and Drug Administration. This product is not intended to diagnose, treat, cure or prevent any disease.

SUGGESTED USE:

One tablet with a full glass of water, five to ten times daily, depending on temperatures and working conditions.

FOR YOUR PROTECTION:

Do not use if printed seal under cap is broken.

WARNING:

If you have or are being treated for heart disease or high blood pressure, consult your physician before using this product. Keep out of the reach of children. Do not use this product if you are on a sodium-restricted diet unless directed by a doctor.

SAFE HANDLING WARNING

Store product at room temperature. Do not expose to excessive heat or moisture.

Comments or questions? Call 1-800-331-0221

If you have any questions or difficulties finding this product, please go to our website: www.numarkbrands.com

PRINCIPAL DISPLAY PANEL

Thermotabs®
Buffered Salt Supplement
100 Tablets
Distributed by Numark Brands, Inc.
P.O. Box 6321, Edison, NJ 08818 Rev 7/16 8P278 KJ C2
Rev 7/16
8P278 KJ C2
T100FC
Lot:
Exp:

Thermotabs®
Buffered Salt Supplement
100 Tablets
Distributed by Numark Brands, Inc.
P.O. Box 6321, Edison, NJ 08818 Rev 7/16 8P278 KJ C2
Rev 7/16
8P278 KJ F2
LOT
EXP